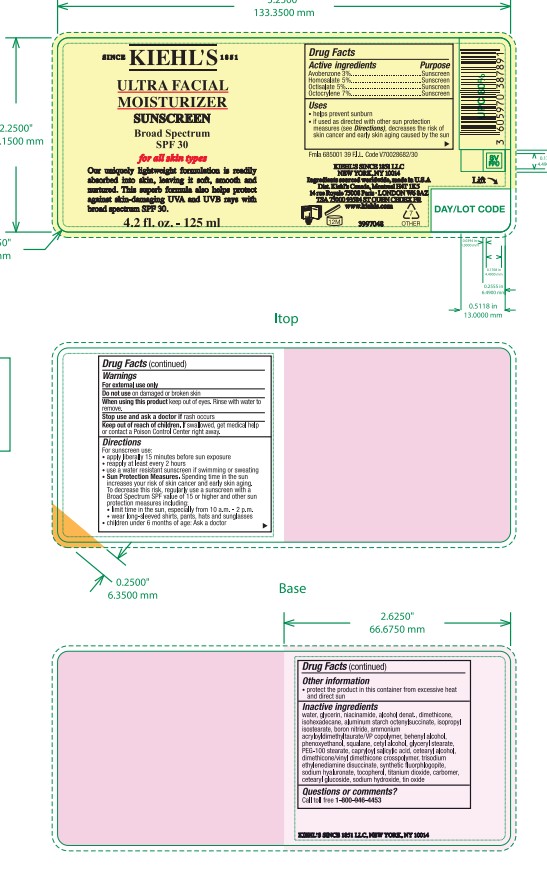 DRUG LABEL: Kiehls Ultra Facial Moisturizer Broad Spectrum SPF 30 Sunscreen
NDC: 49967-894 | Form: LOTION
Manufacturer: L'Oreal USA Products Inc
Category: otc | Type: HUMAN OTC DRUG LABEL
Date: 20240628

ACTIVE INGREDIENTS: Avobenzone 30 mg/1 mL; Homosalate 50 mg/1 mL; Octisalate 50 mg/1 mL; Octocrylene 70 mg/1 mL
INACTIVE INGREDIENTS: WATER; GLYCERIN; NIACINAMIDE; ALCOHOL; DIMETHICONE; ISOHEXADECANE; ALUMINUM STARCH OCTENYLSUCCINATE; ISOPROPYL ISOSTEARATE; BORON NITRIDE; AMMONIUM ACRYLOYLDIMETHYLTAURATE/VP COPOLYMER; DOCOSANOL; PHENOXYETHANOL; SQUALANE; CETYL ALCOHOL; GLYCERYL MONOSTEARATE; PEG-100 STEARATE; CAPRYLOYL SALICYLIC ACID; CETOSTEARYL ALCOHOL; TRISODIUM ETHYLENEDIAMINE DISUCCINATE; HYALURONATE SODIUM; TOCOPHEROL; TITANIUM DIOXIDE; CARBOMER HOMOPOLYMER, UNSPECIFIED TYPE; CETEARYL GLUCOSIDE; SODIUM HYDROXIDE; STANNIC OXIDE

Drug Facts

Active ingredients

Avobenzone 3%

Homosalate 5%

Octisalate 5%

Octocrylene 7%

Purpose

Sunscreen

Uses

- helps prevent sunburn
- if used as directed with other sun protection measures (see Directions), decreases the risk of skin cancer and early skin aging caused by the sun

Warnings

For external use only

Do not use

on damaged or broken skin

When using this product

keep out of eyes. Rinse with water to remove.

Stop use and ask a doctor if

rash occurs

Keep out of reach of children.

If swallowed, get medical help or contact a Poison Control Center right away.

Directions

For sunscreen use:

- apply liberally 15 minutes before sun exposure
- reapply at least every 2 hours
- use a water resistant sunscren if swimming or sweating
- Sun Protection Measures. Spending time in the sun increases your risk of skin cancer and early skin aging. To decrease this risk, regularly use a sunscreen with a Broad Spectrum SPF value of 15 or higher and other sun protection measures including:
- limit time in the sun, especially from 10 a.m. - 2 p.m.
- wear long-sleeved shirts, pants, hats, and sunglasses
- children under 6 months of age: Ask a doctor

Other information

- protect the product in this container from excessive heat and direct sun

Inactive ingredients

water, glycerin, niacinamide, alcohol denat., dimethicone, isohexadecane, aluminum starch octenylsuccinate, isopropyl isostearate, boron nitride, ammonium acryloyldimethyltaurate/VP copolymer, behenyl alcohol, phenoxyethanol, squalane, cetyl alcohol, glyceryl stearate, PEG-100 stearate, capryloyl salicylic acid, cetearyl alcohol, dimethicone/vinyl dimethicone crosspolymer, trisodium ethylenediamine disuccinate, synthetic fluorphlogopite, sodium hyaluronate, tocopherol, titanium dioxide, carbomer, cetearyl glucoside, sodium hydroxide, tin oxide

Questions or comments?

Call toll free 1-800-946-4453